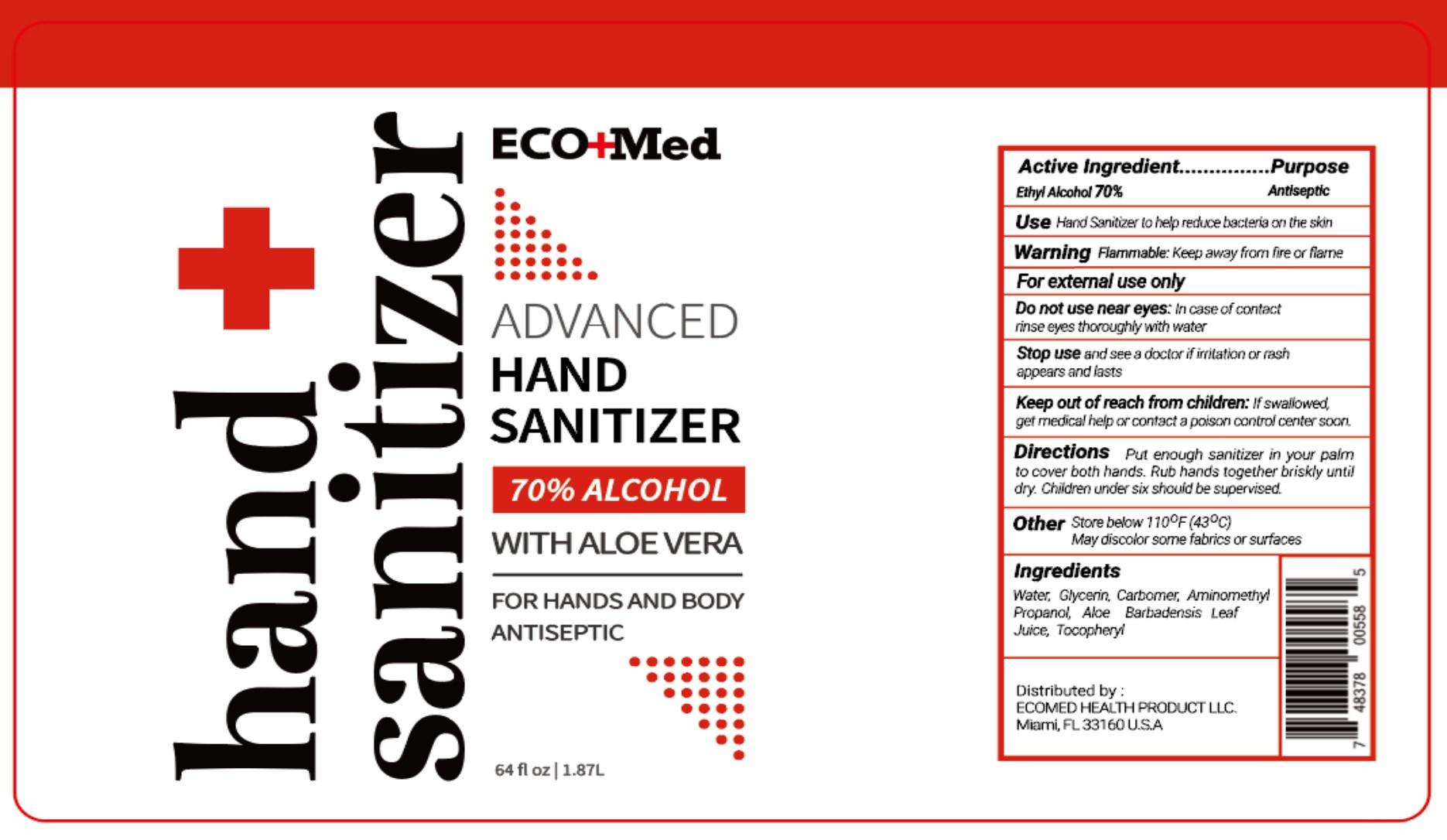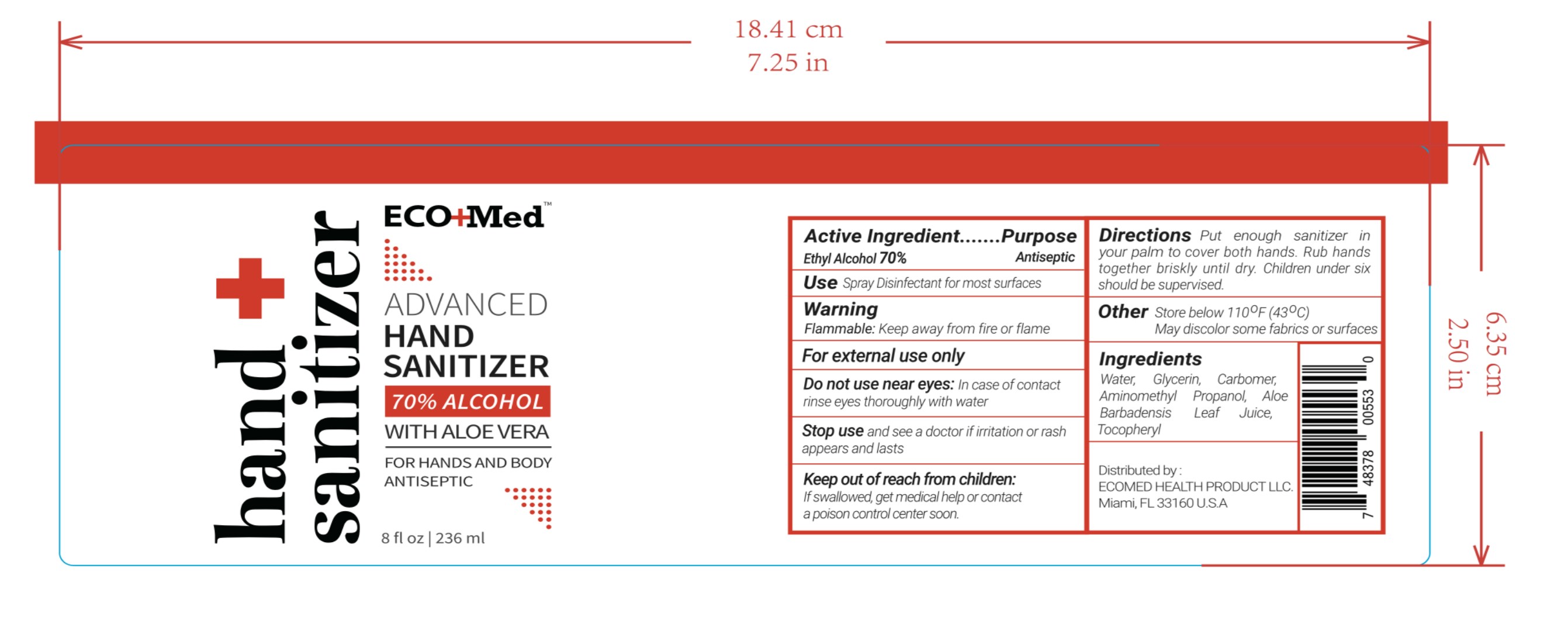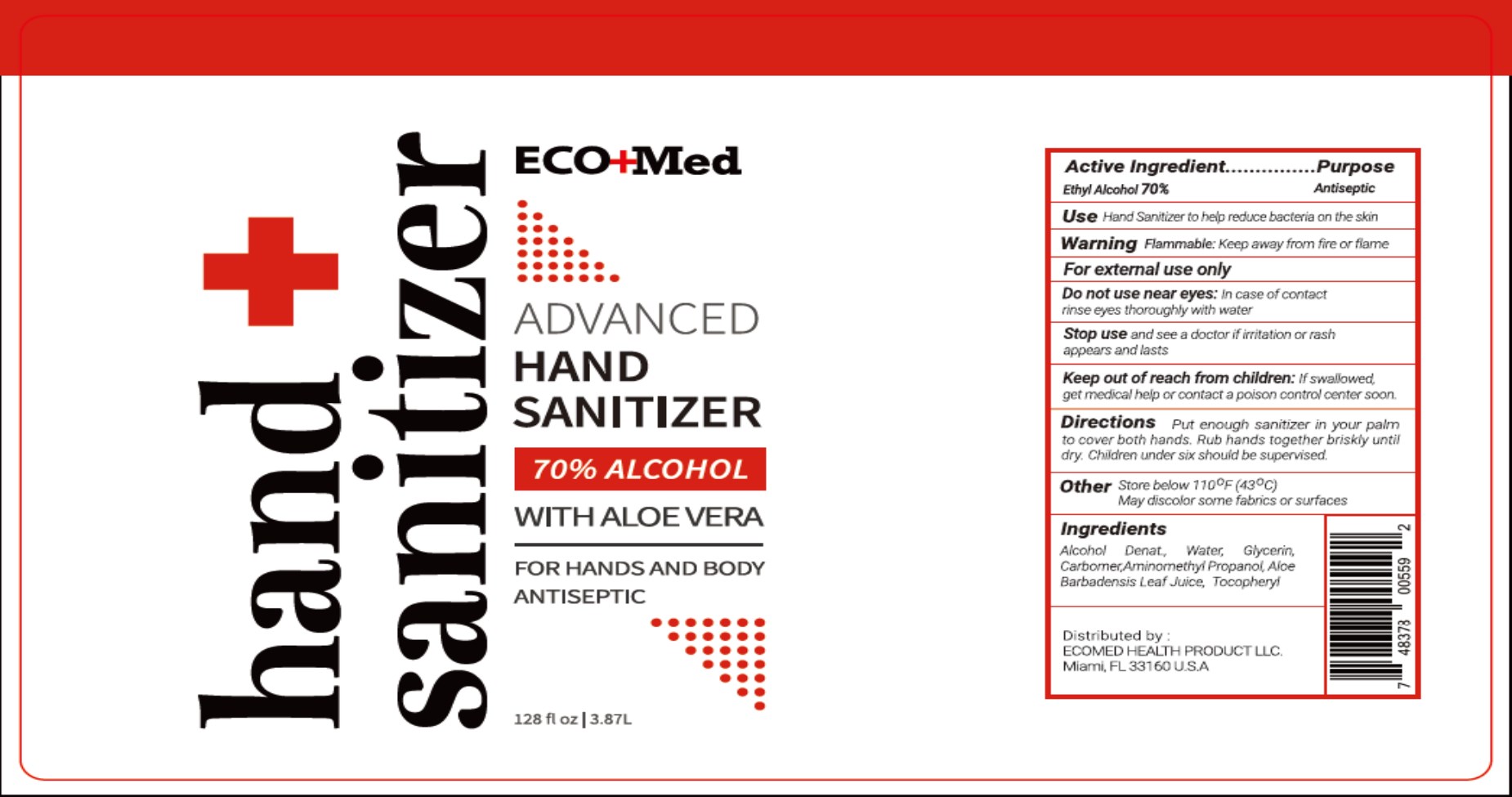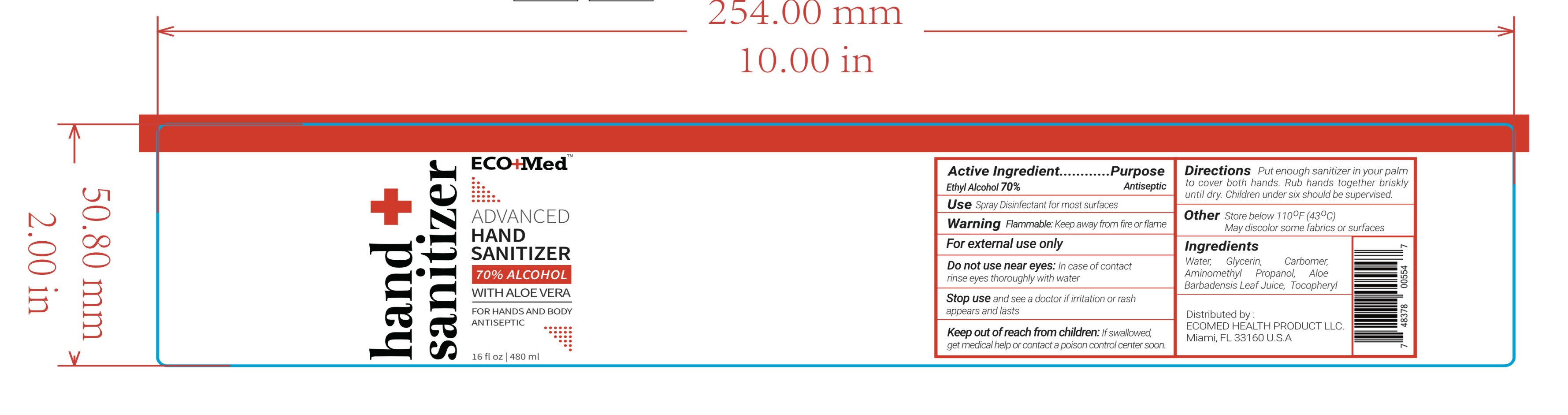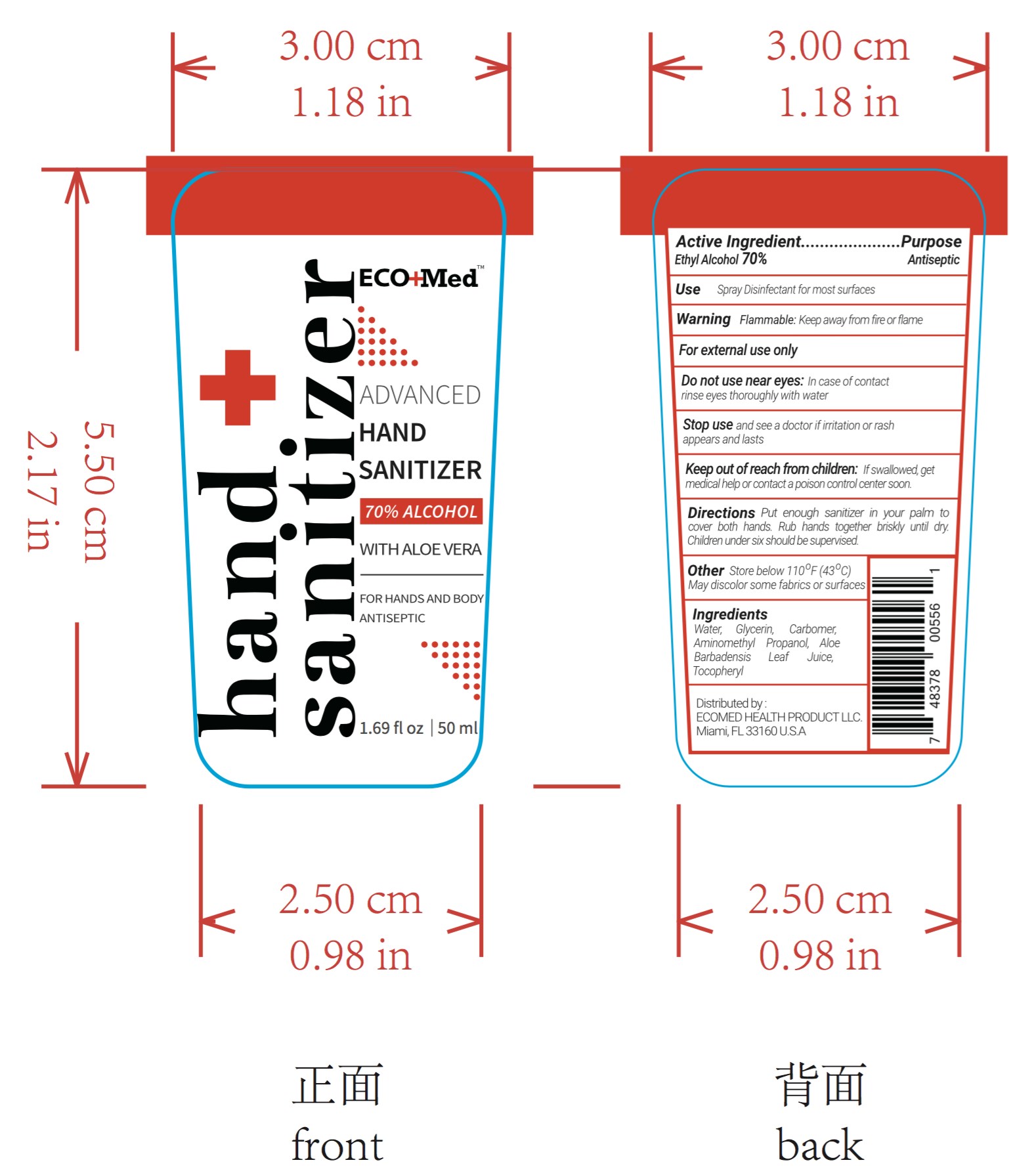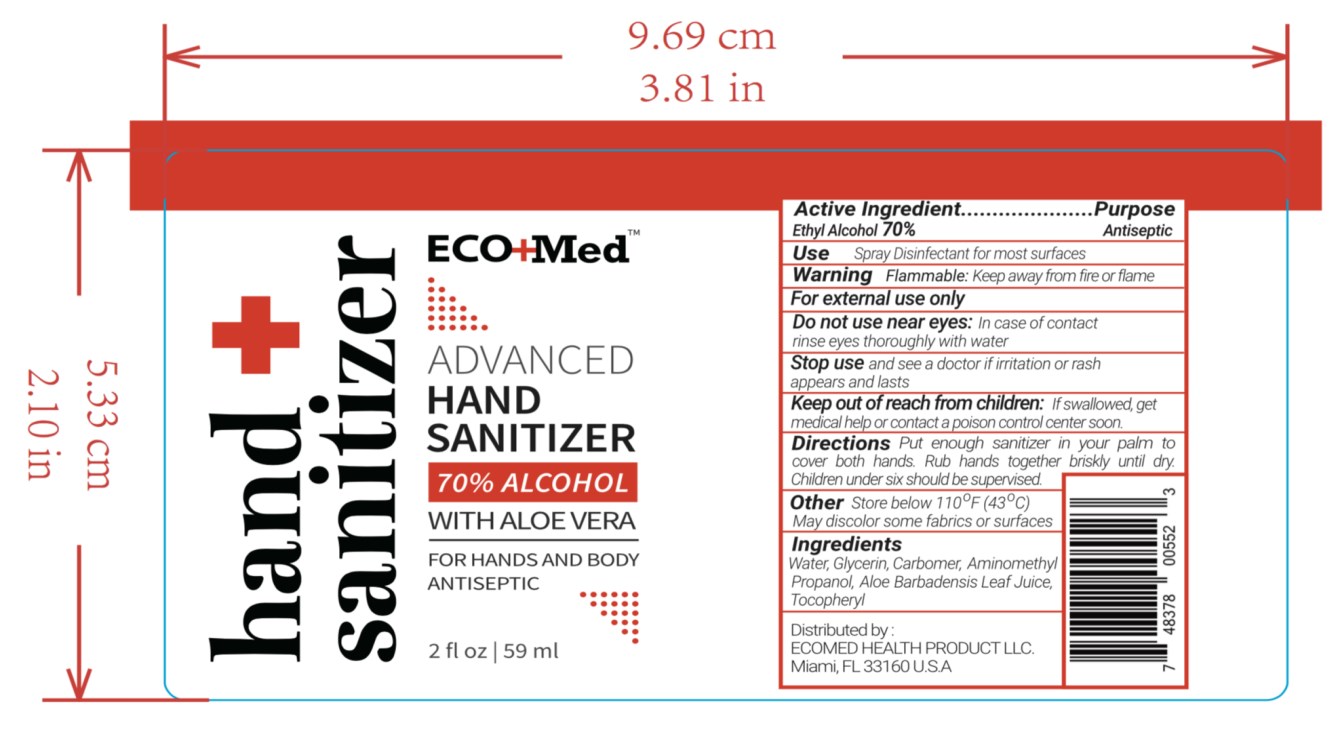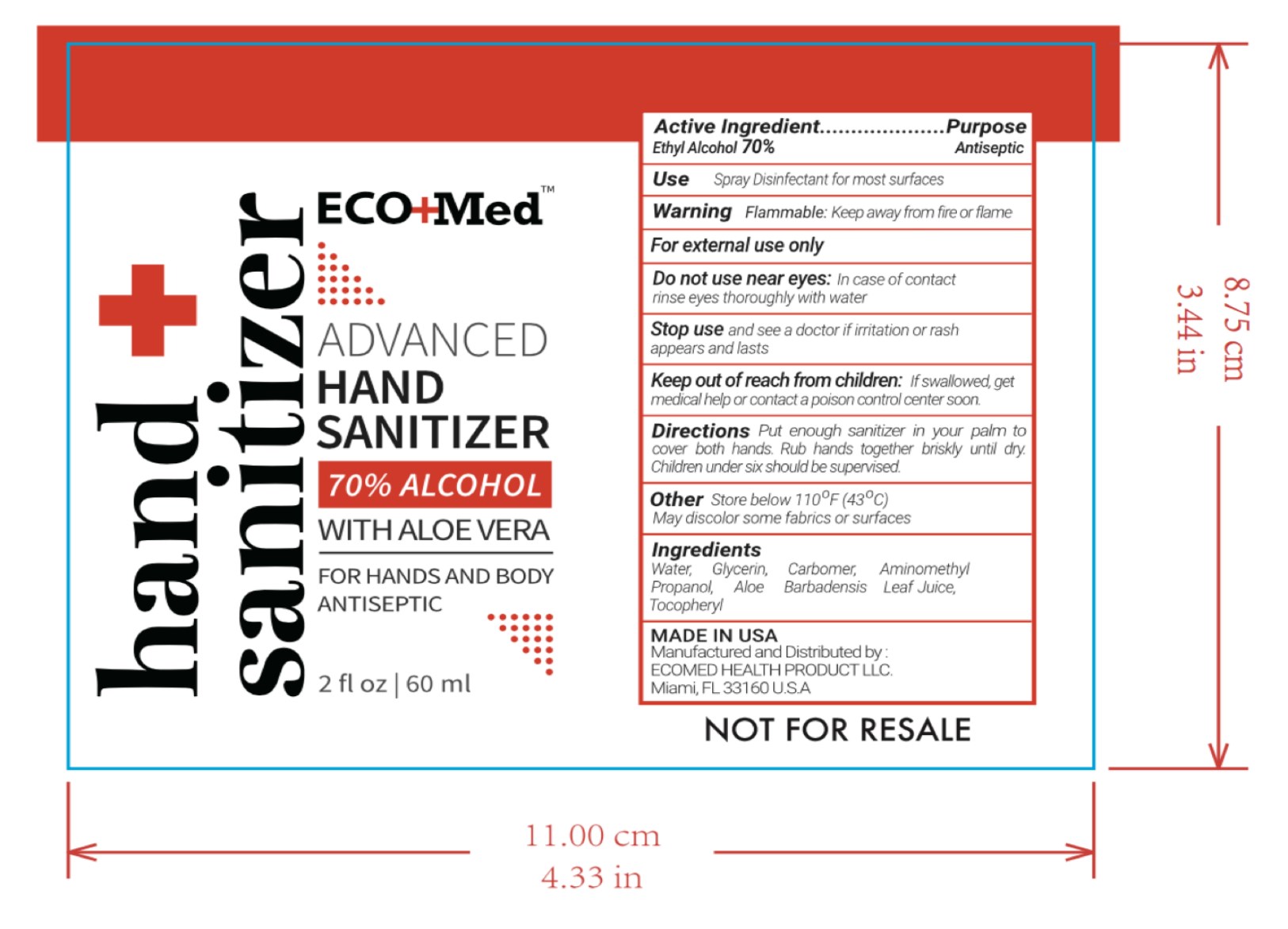 DRUG LABEL: Hand Sanitizer
NDC: 75541-010 | Form: GEL
Manufacturer: Ningbo Meiteli Cosmetic Co., Ltd.
Category: otc | Type: HUMAN OTC DRUG LABEL
Date: 20200814

ACTIVE INGREDIENTS: ALCOHOL 70 mL/100 mL
INACTIVE INGREDIENTS: ALPHA-TOCOPHEROL ACETATE; AMINOMETHYLPROPANOL; GLYCERIN; WATER; ALOE VERA LEAF; CARBOMER COPOLYMER TYPE A (ALLYL PENTAERYTHRITOL CROSSLINKED)

75541-010
Hand Sanitizer

Active Ingredient(s)

Ethyl Alcohol 70%

Purpose

Antiseptic

Use

Hand Sanitizer to help reduce bacteria on the skin.

Warning

Flammable. Keep away from heat or flame

For external use only.

Do not use near eyes

In case of contact rinse eyes thoroughly with water.

Stop use

Stop use and see a doctor if imtation or rash appears and lasts

Keep out of reach of children. If swallowed, get medical help or contact a poison control Center right away.

Directions

Put enough sanitizer in your palm to cover both hands. Rub hands together briskly until dry. Children under six should be supervised.

Other

Store below 710 °F (43 °C)
May discolor some fabrics or surfaces

Inactive ingredients

Water, Glycerin, Carbomer,Aminomethyl Propanol, Aloe Barbadensis Leaf Juice, Tocopheryl

Do not use near eyes: In case of contact rinse eyes thoroughly with water

Stop use and see a doctor if irritation or rash appears and lasts

Keep out of reach from children: If swallowed, get medical help or contact a poison control center soon.